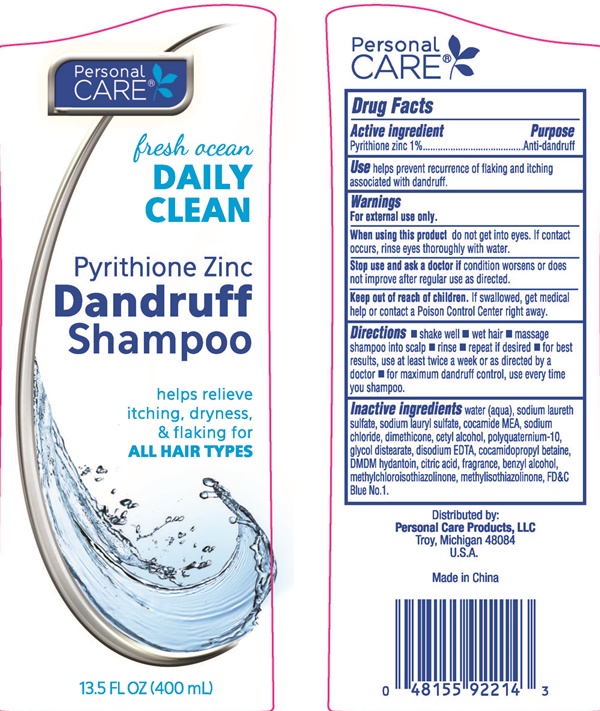 DRUG LABEL: Personal Care Pyrithione Zinc Dandruff
                
NDC: 29500-6000 | Form: SHAMPOO
Manufacturer: Personal Care Products, Inc.
Category: otc | Type: HUMAN OTC DRUG LABEL
Date: 20160629

ACTIVE INGREDIENTS: PYRITHIONE ZINC 1 g/100 mL
INACTIVE INGREDIENTS: WATER; SODIUM LAURETH SULFATE; SODIUM LAURYL SULFATE; SODIUM CHLORIDE; GLYCOL DISTEARATE; EDETATE DISODIUM; COCAMIDOPROPYL BETAINE; CITRIC ACID MONOHYDRATE; BENZYL ALCOHOL; METHYLISOTHIAZOLINONE; FD&C BLUE NO. 1

Drug Facts Active Ingredient

Pyrithione Zinc 1%

Purpose

Anti-dandruff

Keep out of reach of children.

If swallowed, get medical help or contact a Poison Control Center right away.

Use

helps prevent recurrence of flaking and itching associated with dandruff.

Warnings

For external use only.

When using this product

do not get into eyes. If contact occurs, rinse eyes thoroughly with water.

Stop use and ask a doctor if

condition worsens or does not improve after regular use as directed.

Directions

- shake well
- wet hair
- massage shampoo into scalp
- rinse
- repeat if desired
- for best results, use at least twice a week or as directed by a doctor
- for maximum dandruff control, use every time you shampoo

Inactive ingredients

water (aqua), sodium laureth sulfate, sodium lauryl sulfate, cocamide MEA, sodium chloride, polyquaternium-7,
glycol distearate, disodium EDTA, cocamidopropyl betain, DMDM hydantoin guar hydropropyltrimonium chloride,
citric acid, fragrance, benzyl alcohol, methylchloroisothiazolinone, methylisothiazolinone, FD and C Blue #1.

Personal care Dandruff Shampoo

Personal Care®

fresh ocean

DAILY CLEAN
Pyrithione Zinc

Dandruff
Shampoo
helps to relieve itching,
dryness & flaking for

ALL HAIR TYPES

13.5 FL. OZ. (400 mL)
Distributed by:
Personal Care Products, LLC
Troy, Michigan 48025

U.S.A.

Made in China